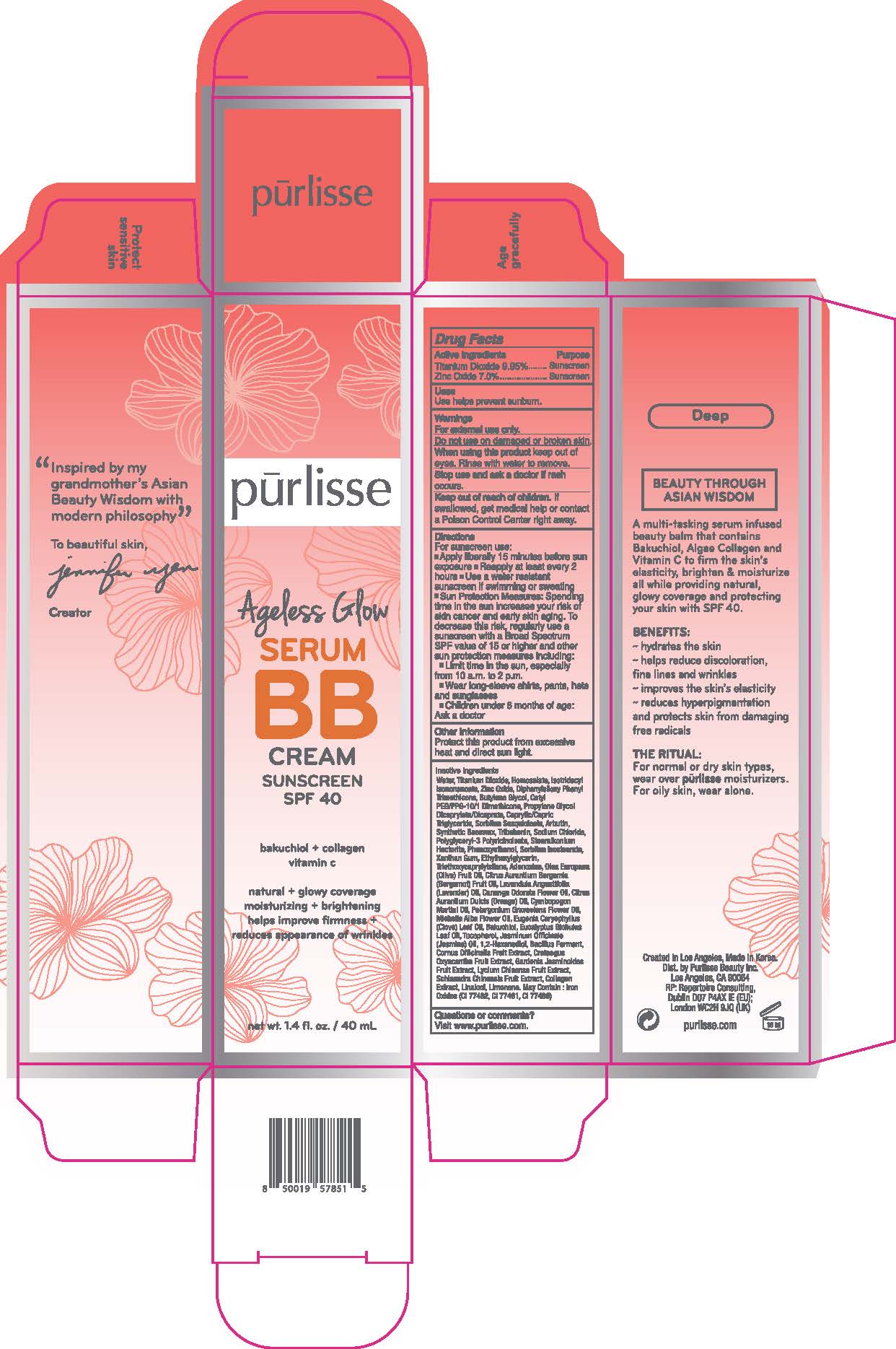 DRUG LABEL: Ageless Glow Serum BB Cream Sunscreen SPF 40 - Deep
NDC: 72407-430 | Form: CREAM
Manufacturer: Pur-lisse Beauty, LLC
Category: otc | Type: HUMAN OTC DRUG LABEL
Date: 20251230

ACTIVE INGREDIENTS: ZINC OXIDE 7 g/100 mL; TITANIUM DIOXIDE 5.09 g/100 mL; HOMOSALATE 9.5 g/100 mL
INACTIVE INGREDIENTS: CORNUS OFFICINALIS FRUIT; SYNTHETIC BEESWAX; XANTHAN GUM; STEARALKONIUM HECTORITE; TOCOPHEROL; TRIETHOXYCAPRYLYLSILANE; MICHELIA ALBA FLOWER OIL; EUGENIA CARYOPHYLLUS (CLOVE) LEAF OIL; PROPYLENE GLYCOL DICAPRYLATE/DICAPRATE; BAKUCHIOL; CANANGA ODORATA FLOWER OIL; SODIUM CHLORIDE; LYCIUM CHINENSE FRUIT; PHENOXYETHANOL; LINALOOL, (+/-)-; CITRUS AURANTIUM BERGAMIA (BERGAMOT) FRUIT OIL; TRIBEHENIN; OLEA EUROPAEA (OLIVE) FRUIT OIL; CAPRYLIC/CAPRIC TRIGLYCERIDE; SORBITAN ISOSTEARATE; CYMBOPOGON MARTINI OIL; EUCALYPTUS GLOBULUS LEAF OIL; BUTYLENE GLYCOL; CITRUS AURANTIUM DULCIS (ORANGE) OIL; LAVANDULA ANGUSTIFOLIA (LAVENDER) OIL; SCHISANDRA CHINENSIS FRUIT; BACILLUS POLYFERMENTICUS; ARBUTIN; ADENOSINE; GARDENIA JASMINOIDES FRUIT; LIMONENE, (+)-; SORBITAN SESQUIOLEATE; 1,2-HEXANEDIOL; ISOTRIDECYL ISONONANOATE; DIPHENYLSILOXY PHENYL TRIMETHICONE; CETYL PEG/PPG-10/1 DIMETHICONE (HLB 2); JASMINUM OFFICINALE FLOWER; WATER; POLYGLYCERYL-3 PENTARICINOLEATE; MARINE COLLAGEN, SOLUBLE; CRATAEGUS LAEVIGATA FRUIT; PELARGONIUM GRAVEOLENS FLOWER OIL; ETHYLHEXYLGLYCERIN

Drug Facts

Active Ingredients

Homosalate 9.5%

Titanium Dioxide 5.09%

Zinc Oxide 7.0%

Purpose

Sunscreen

Uses

Use helps prevent sunburn.

Warnings

For external use only.

Do not use on damage or broken skin.

When using this product keep out of eyes. Rinse with water to remove.

Stop use and ask a doctor if rash occurs.

Keep out of reach of children. If swallowed, get medical help or contact a Poison Control Center right away.

Directions

For sunscreen use:

- Apply liberally 15 minutes before sun exposure
- Reapply at least every 2 hours
- Use a water resistant sunscreen if swimming or sweating
- Sun Protection Measures: Spending time in the sun increases your risk of skin cancer and early skin aging. To decrease this risk, regularly use a sunscreen with a Broad Spectrum SPF value of 15 or higher and other sun protection measures including:
- Limit time in the sun, especially from 10 a.m. to 2 p.m.
- Wear long-sleeve shirts, pants, hats and sunglasses
- Children under 6 months of age: Ask a doctor

Other Information

Protect this product from excessive heat and direct sun light.

Inactive Ingredients

Water, Isotridecyl Isononanoate, Diphenylsiloxy Phenyl Trimethicone, Butylene Glycol, Cetyl PEG/PPG-10/1 Dimethicone,Propylene Glycol Dicaprylate/Dicaprate, Caprylic/Capric Triglyceride, Sorbitan Sesquioleate, Synthetic Beeswax, Arbutin, Sodium Chloride, Tribehenin, Polyglyceryl-3 Polyricinoleate, Stearalkonium Hectorite, Phenoxyethanol, Sorbitan Isostearate, Xanthan Gum, Ethylhexylglycerin, Triethoxycaprylylsilane, Adenosine, Olea Europaea (Olive) Fruit Oil, Citrus Aurantium Bergamia (Bergamot) Fruit Oil, Lavandula Angustifolia (Lavender) Oil, Cananga Odorata Flower Oil, Citrus Aurantium Dulcis (Orange) Oil, Pelargonium Graveolens Flower Oil, Cymbopogon Martini Oil, Michelia Alba Flower Oil, Eugenia Caryophyllus (Clove) Leaf Oil, Bakuchiol, Eucalyptus Globulus Leaf Oil, Tocopherol, Jasminum Officinale (Jasmine) Oil, 1,2-Hexanediol, Bacillus Ferment, Cornus Officinalis Fruit Extract, Crataegus Oxyacantha Fruit Extract, Lycium Chinense Fruit Extract, Gardenia Jasminoides Fruit Extract, Schisandra Chinensis Fruit Extract, Collagen Extract, Linalool, Limonene. May Contain: Iron Oxides (CI 77492, CI 77491, CI 77499)

Questions or comments?

Visit www.purlisse.com.

Principal Display Panel - Ageless Glow Serum BB Cream Sunscreen SPF 40 - Deep

pūrlisse

Ageless Glow

Serum

BB

CREAM

SUNSCREEN

SPF 40

bakuchiol + collagen

vitamin c

natural + glowy coverage

moisturizing + brightening

helps improve firmness +

reduces appearance of

wrinkles

1.4 fl. oz. / 40 mL